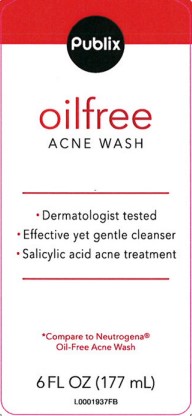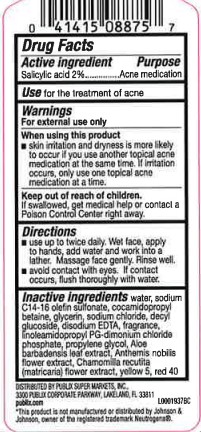 DRUG LABEL: Oil Free Acne Wash
NDC: 56062-947 | Form: LOTION
Manufacturer: Publix Super Markets, Inc.
Category: otc | Type: HUMAN OTC DRUG LABEL
Date: 20260205

ACTIVE INGREDIENTS: SALICYLIC ACID 20.6 mg/1 mL
INACTIVE INGREDIENTS: WATER; SODIUM C14-16 OLEFIN SULFONATE; COCAMIDOPROPYL BETAINE; GLYCERIN; SODIUM CHLORIDE; DECYL GLUCOSIDE; EDETATE DISODIUM ANHYDROUS; LINOLEAMIDOPROPYL PROPYLENE GLYCOL-DIMONIUM CHLORIDE PHOSPHATE; PROPYLENE GLYCOL; ALOE VERA LEAF; CHAMAEMELUM NOBILE FLOWER; CHAMOMILE; FD&C YELLOW NO. 5; FD&C RED NO. 40

Publix 947.003/947AC-AD
Oil Free Acne Wash

Active ingredient

Salicylic acid 2%

Purpose

Acne medication

Use

for the treatment of acne

Warnings

For external use only

When using this product

- skin irritation and dryness is more likely to occur if you use another topical acne medication at the same time. If irritation occurs, only use one topical acne medication at a time

Keep out of reach of children.

If swallowed, get medical help or contact a Poison Control Center right away.

Directions

- use twice a daily. Wet face, apply to hands, add water and work into lather. Massage face gently. Rinse well.
- avoid contact with eyes. If contact with eyes. If contact occurs, flush thoroughly with water.

Inactive ingredients

water, sodium C14-16 olefin sulfonate, cocamidopropyl betaine, glycerin, sodium chloride, decyl glucoside, disodium EDTA, fragrance, linoleamidopropyl PG-dimonium chloride phosphate, propylene glycol, Aloe barbadensis leaf extract, Anthemis nobilis flower extract, Chamomilla recutita (matricaria) flower extract, yellow 5, red 40

Disclaimer

*This product is not manufactured or distributed by Johnson & Johnson, owner of the registered trademark Neutrogena.

Adverse Reactions Section

DISTRIBUTED BY: PUBLIX SUPER MARKETS, INC.,

3300 PUBLIX CORPORATE PARKWAY, LAKELAND, FL 33811

publix.com

principal display panel

Publix

oilfree

ACNE WASH

- Dermatologist tested
- Effective yet gentle cleanser
- Salicylic acid acne treatment

*Compare to Neutrogena®Oil-Free Acne Wash

6 FL OZ (177 mL)